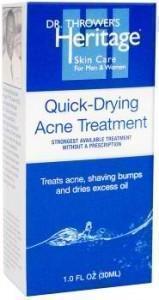 DRUG LABEL: QUICK DRY ACNE TREATMENT
NDC: 69299-101 | Form: LOTION
Manufacturer: DR. THROWER'S SKINCARE, INC.
Category: otc | Type: HUMAN OTC DRUG LABEL
Date: 20141202

ACTIVE INGREDIENTS: SULFUR 10 g/100 mL
INACTIVE INGREDIENTS: ZINC OXIDE; ALCOHOL; WATER; FILIPENDULA ULMARIA WHOLE; CAMPHOR OIL; MAGNESIUM ALUMINUM SILICATE; FERRIC OXIDE YELLOW; FERROSOFERRIC OXIDE; FERRIC OXIDE RED; PEG-8 DIMETHICONE; GLYCERIN; OCTYLDODECANOL; VITAMIN A PALMITATE; .ALPHA.-TOCOPHEROL ACETATE; ASCORBIC ACID; PYRIDOXINE HYDROCHLORIDE; SILICON DIOXIDE; SODIUM PROPOXYHYDROXYPROPYL THIOSULFATE SILICA; CHOLECALCIFEROL

ACTIVE INGREDIENTS:

SULFUR- 10.0%

ZINC OXIDE- 5.0%

PURPOSE:

TREATS ACNE AND SHAVE BUMPS

USES:

- DRIES UP EXCESS OIL

- CLEARS UP ACNE AND SHAVING BUMPS

DIRECTIONS:

USE EVENINGS. SHAKE TO ACTIVATE

APPLY TO CLEAN SKIN AFTER SPF 30 IN AM OR ALOE MOISTURIZING CREAM IN PM

APPLY DIRECTLY TO THE ACNE OR SHAVING BUMPS WITH A COTTON SWAB.

ALLOW TO DRY FOR APPROXIMATELY 5-10 MINTUES AND LEAVE ON OVERNIGHT.

INACTIVE INGREDIENTS:

ETHYL ALCOHOL, AQUA, SPIRAEA ULMARIA EXTRACT, CINNAMOMUM CAMPHORA OIL, MAGNESIUM ALUMINIUM SILICATE, PIGMENT YELLOW 42, PIGMENT BLACK11, PIGMENT RED 101, PEG-8 DIMETHICONE, GLYCERINE, OCTYLDODECANOL, RETINYL PALMITATE (VITAMIN A), TOCOPHERYL ACETATE (VITAMIN E), ASCORBIC ACID (VITAMIN C), PYRIDOXINE HCL (VITAMIN B6), SILICA, SODIUM PROPOXYHYDROXYPROPYL THIOSULFATE SILICA, CHOLECALCIFEROL

KEEP OUT OF REACH OF CHILDREN.

WARNINGS

FOR EXTERNAL USE ONLY